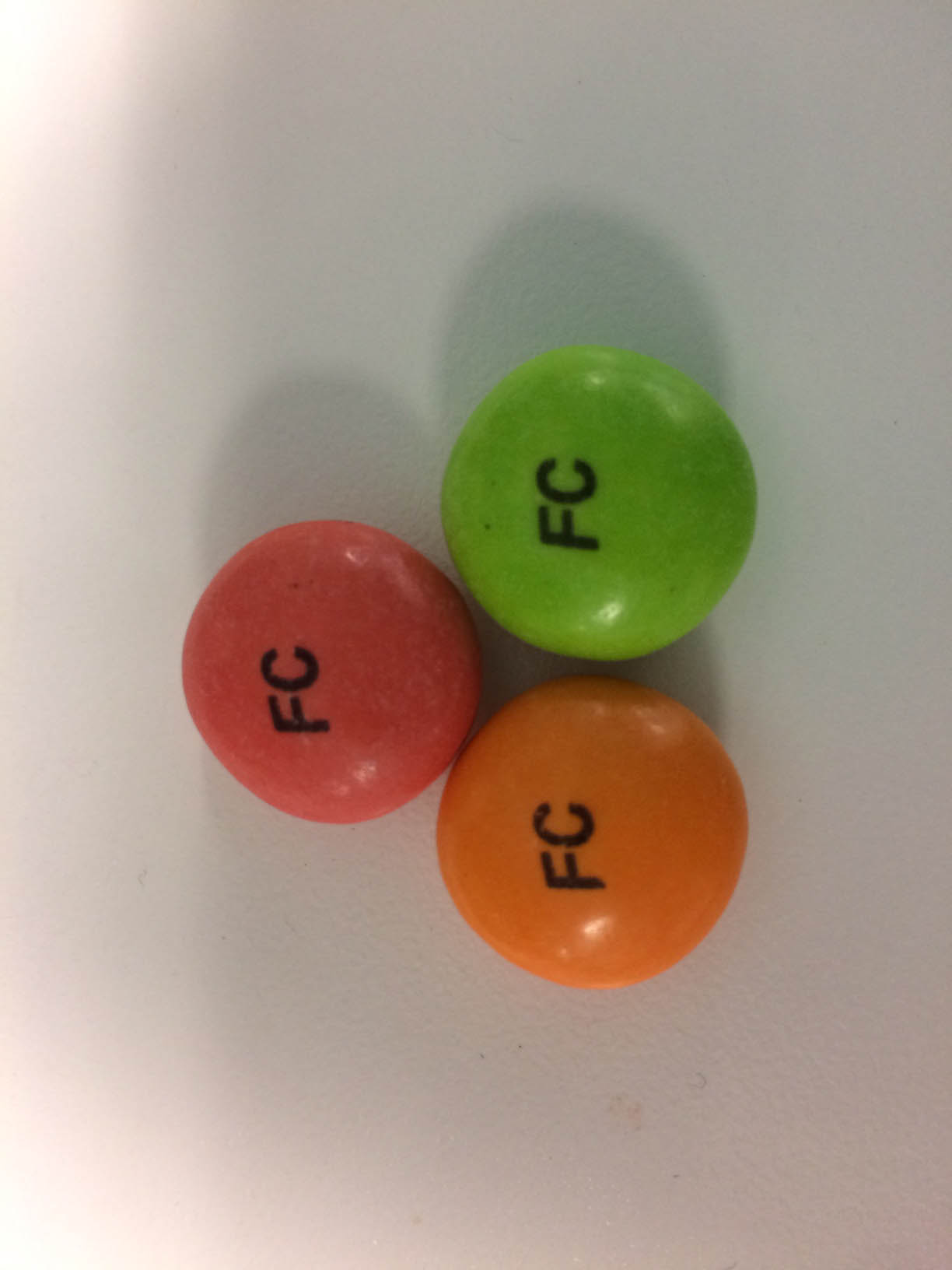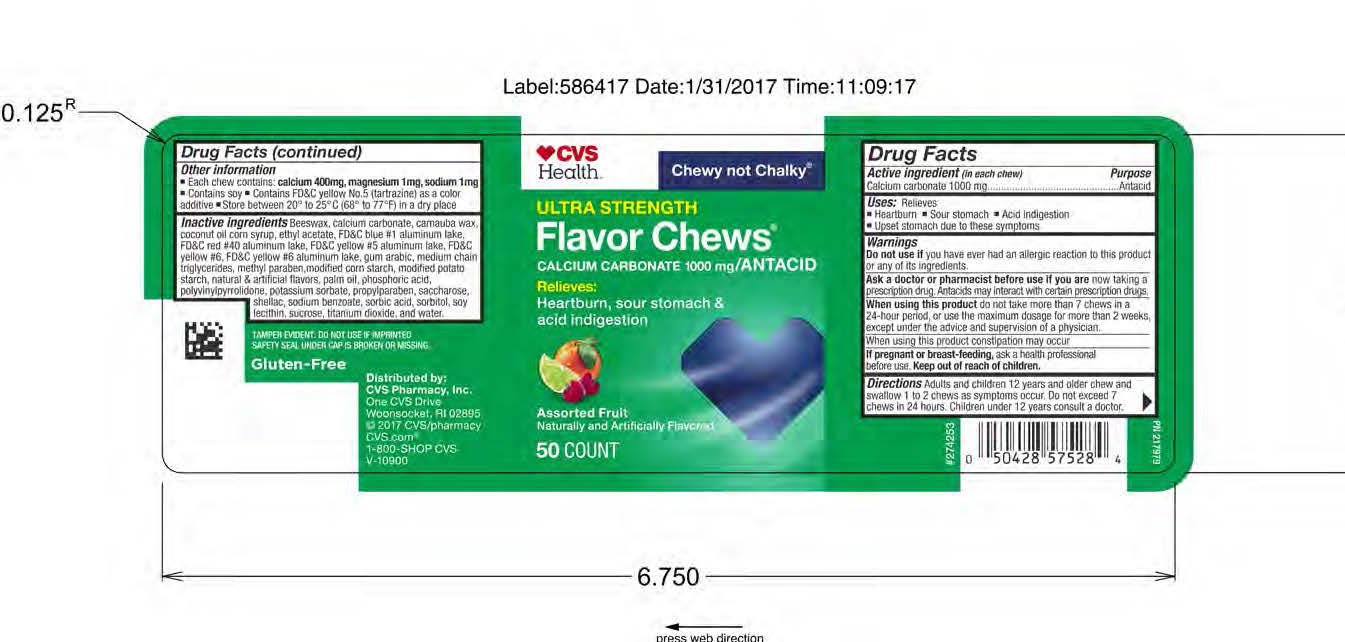 DRUG LABEL: Antacid Fruit Chew
NDC: 69842-361 | Form: TABLET, CHEWABLE
Manufacturer: CVS Pharmacy
Category: otc | Type: HUMAN OTC DRUG LABEL
Date: 20170310

ACTIVE INGREDIENTS: CALCIUM CARBONATE 1000 mg/1 1
INACTIVE INGREDIENTS: WATER

Calcium Carbonate 1000 mg

Active ingredient (in each chew)

Calcium Carbonate 1000 mg

Purpose

Antacid

INDICATIONS AND USAGE

Uses: Relieves

Heartburn

Sour stomach

Acid indigestion

Upset stomach due to these symptoms

Warnings

Do not use if you have ever had an allergic reaction to this product or any of its ingredients.

Ask a doctor or pharmacist before use if you are now taking a prescription drug. Antacids may interact with certain prescription drugs.

When using this product do not take more than 7 chews in a 24-hour period, or use the maximum dosage for more than 2 weeks, except under the advice and supervision of a physician.

When using this product constipation may occur.

INACTIVE INGREDIENT

If pregnant of breast-feeding, ask a health professional before use.

Keep out of reach of children.

Directions

Adults and children 12 years and older chew and swallow 1 to 2 chews as symptoms occur. Do not exceed 7 chews in 24 hours.

Children under 12 years consult a doctor.

OTHER SAFETY INFORMATION

Each chew contains: calcium 400mg, magnesium 1mg, sodium 1mg

Contains soy

Contains FD&C yellow No. 5 (tartrazine) as a color additive

INACTIVE INGREDIENT

Inactive ingredients: Beeswax, calcium carbonate, carnauba wax, coconut oil, corn syrup, ethyl acetate, FD&C blue no. 1 aluminum lake, FD&C red no. 40 aluminum lake, FD&C yellow no. 5 aluminum lake, FD&C yellow no. 6, FD&C yellow no. 6 aluminum lake, gum arabic, medium chain triclycerides, methyl paraben, modified corn starch, modified potato starch, natural and artificial flavors, palm oil, phosphoric acid, polyvinylpyrrolidone, potassium sorbate, propyl paraben, saccharose, shellac, sodium benzoate, sorbic acid, sorbitol, soy lecithin, sucrose, titanium dioxide, and water.

QUESTIONS

Questions? Call 1-800-245-2898 Monday through Friday, 9AM - 4PM EST